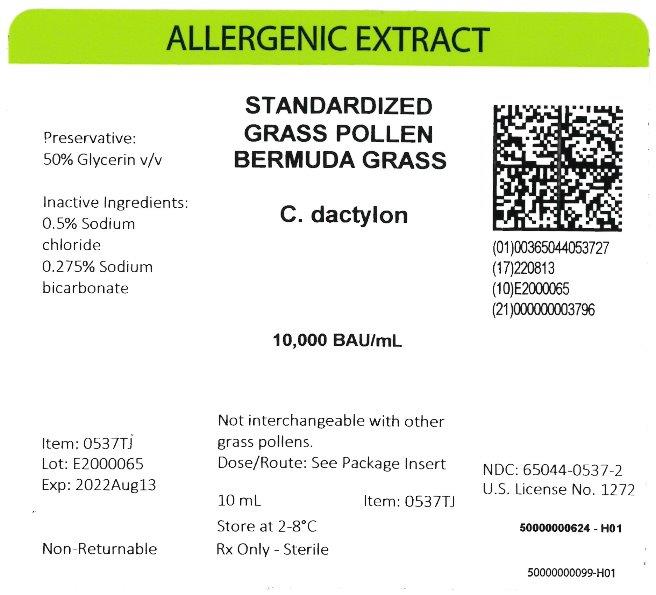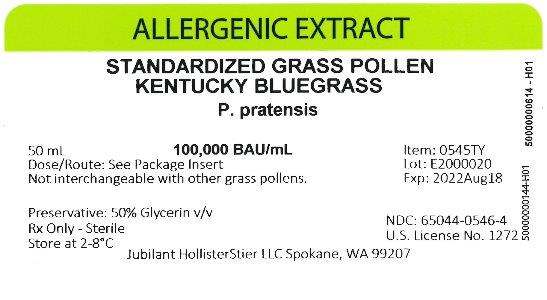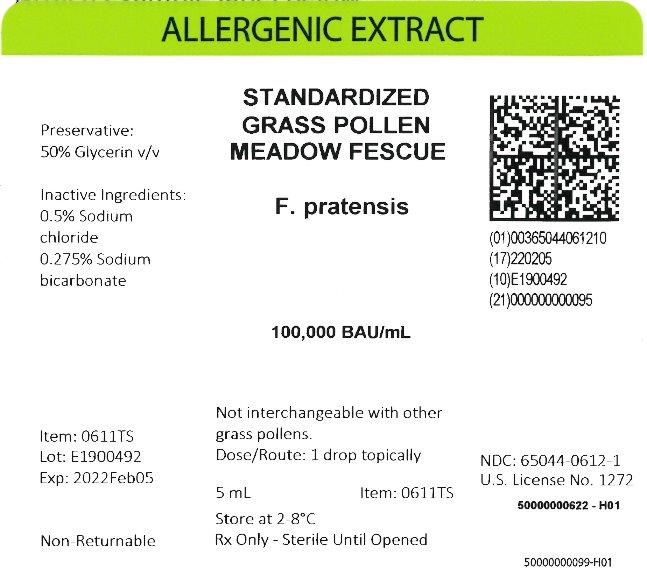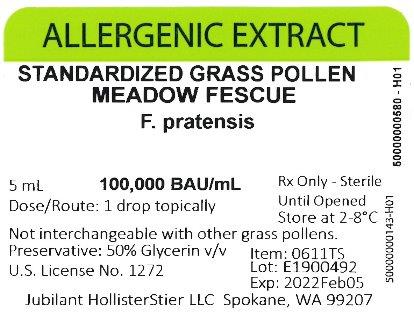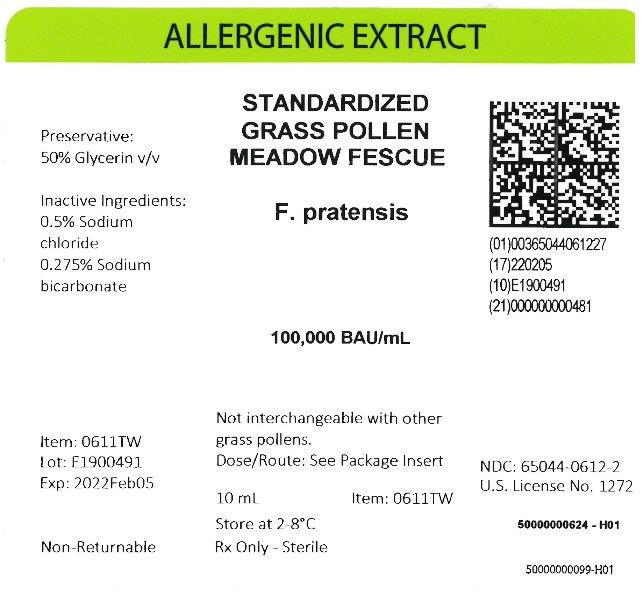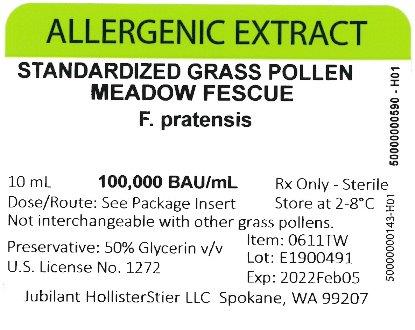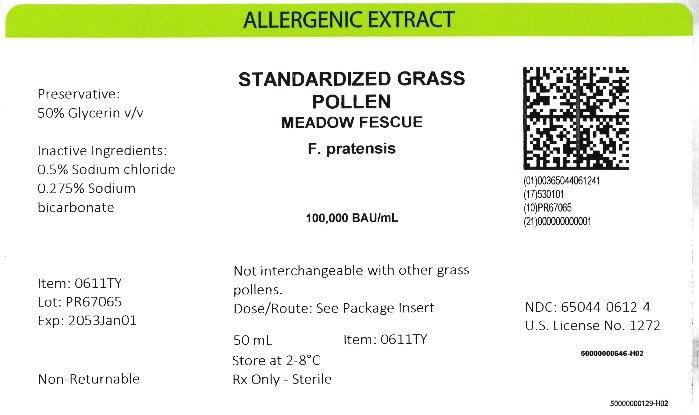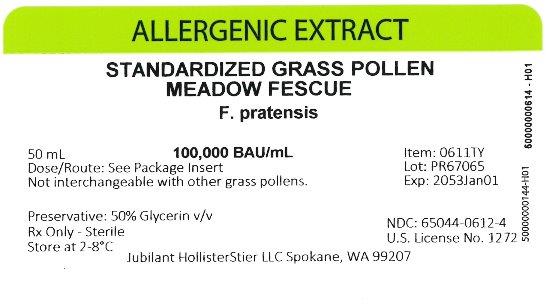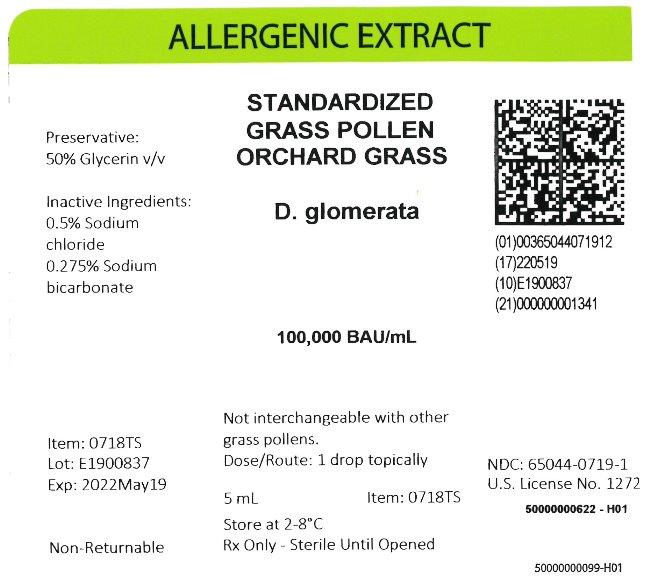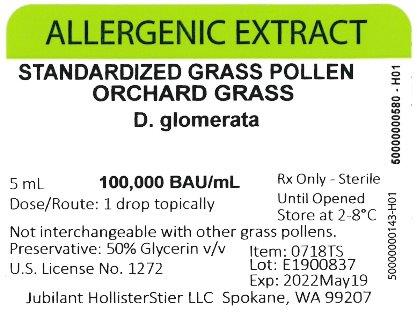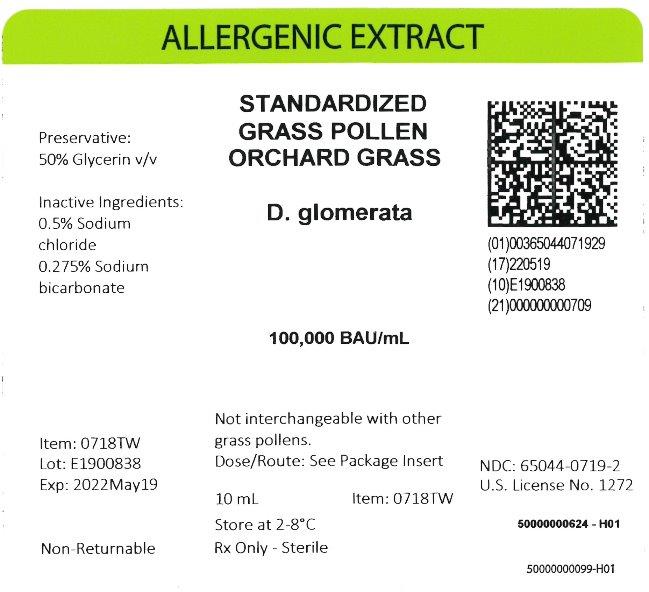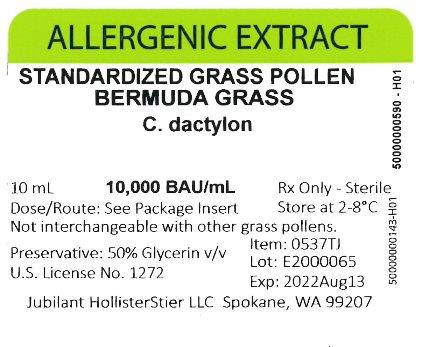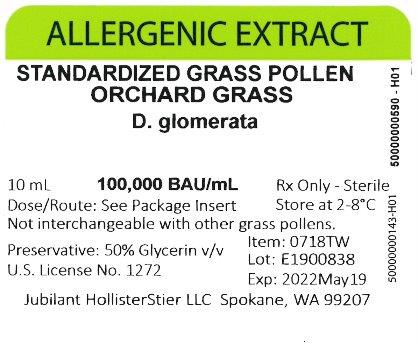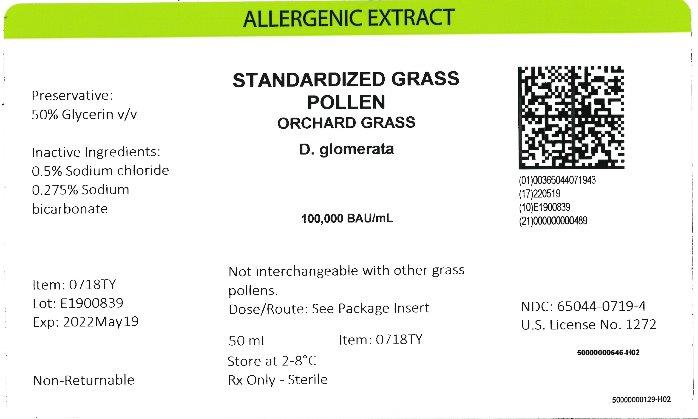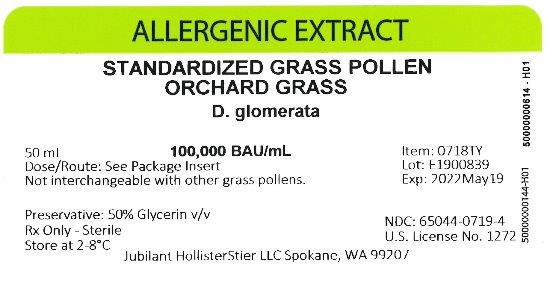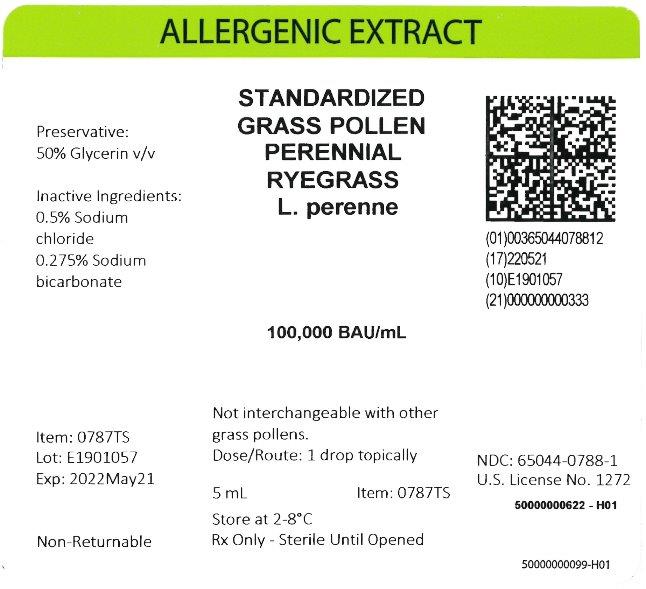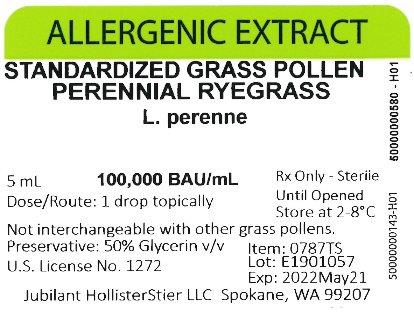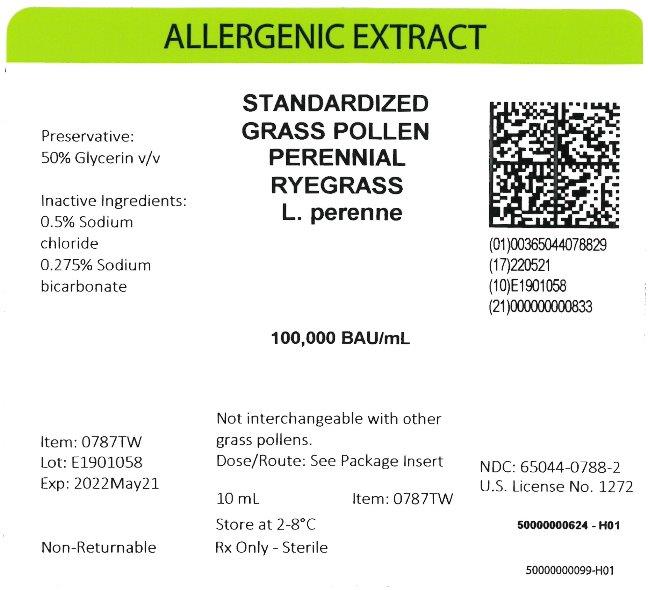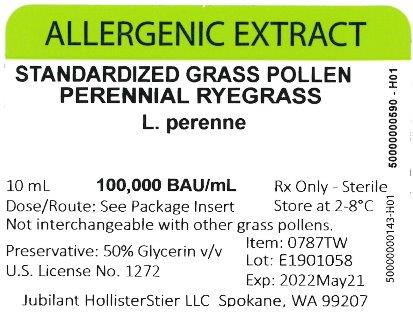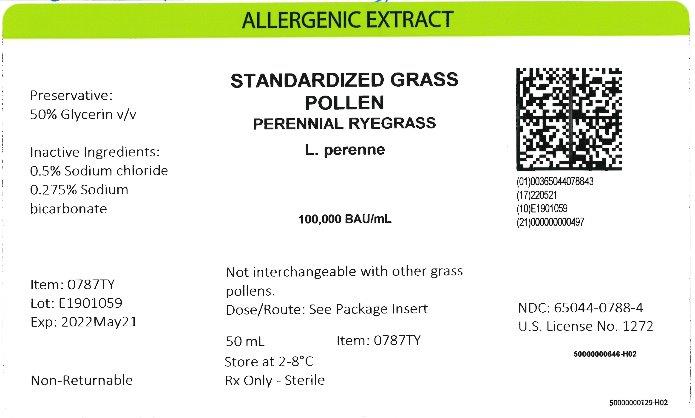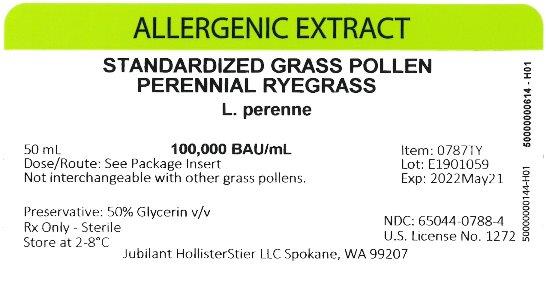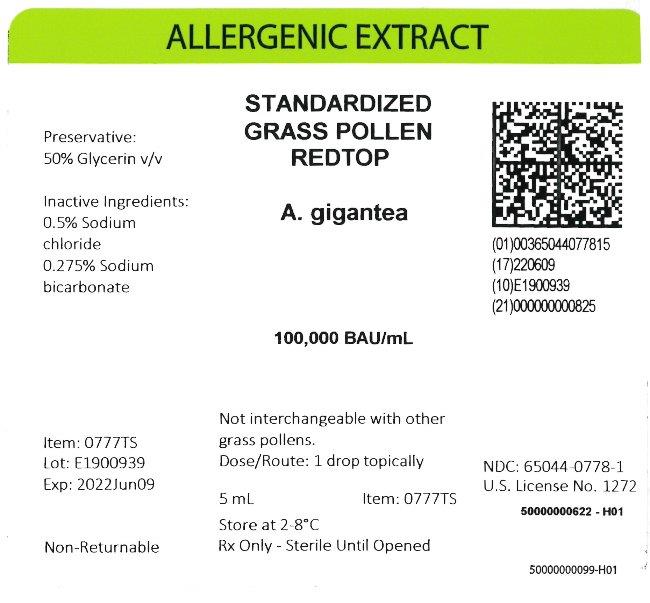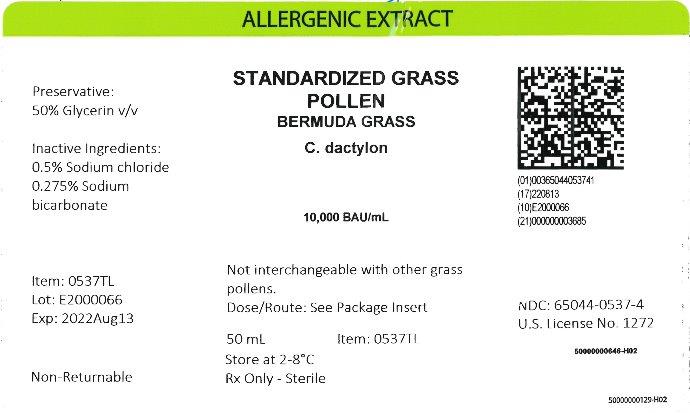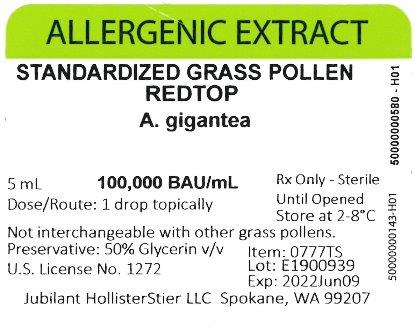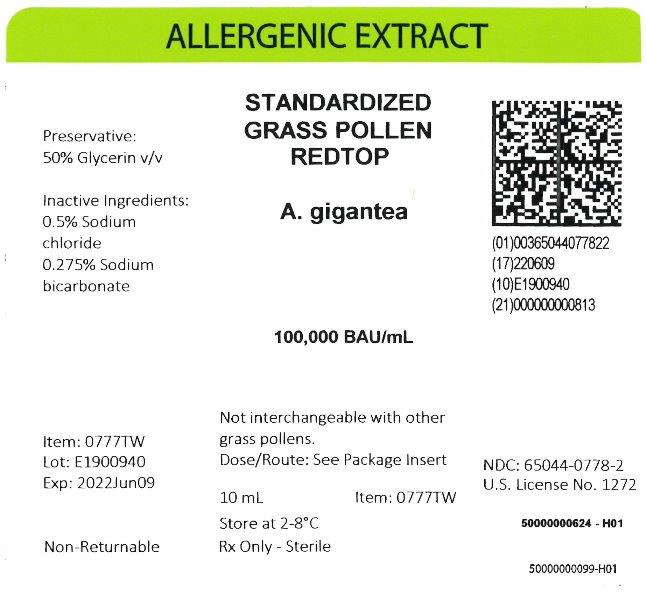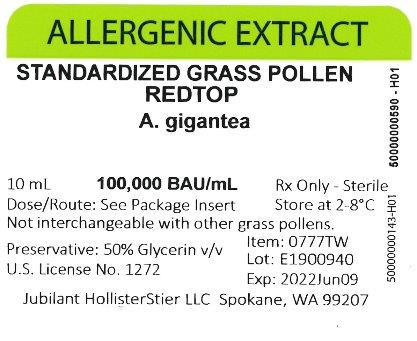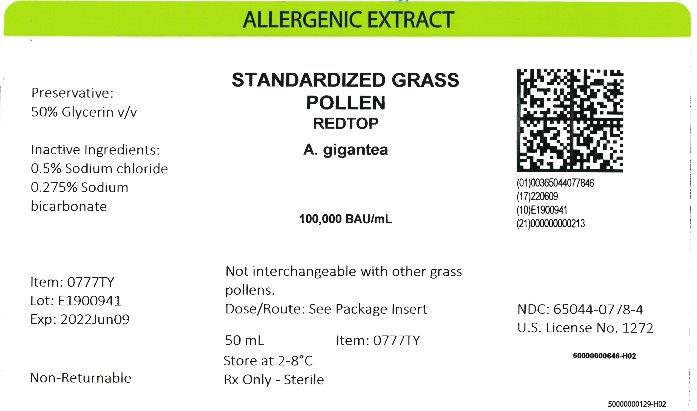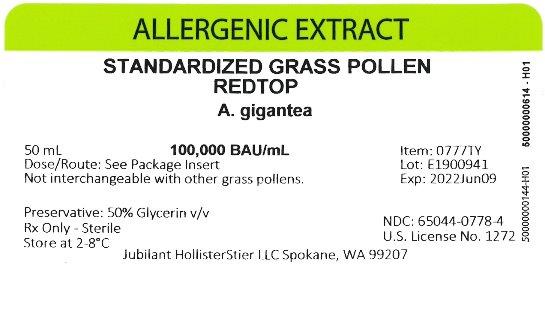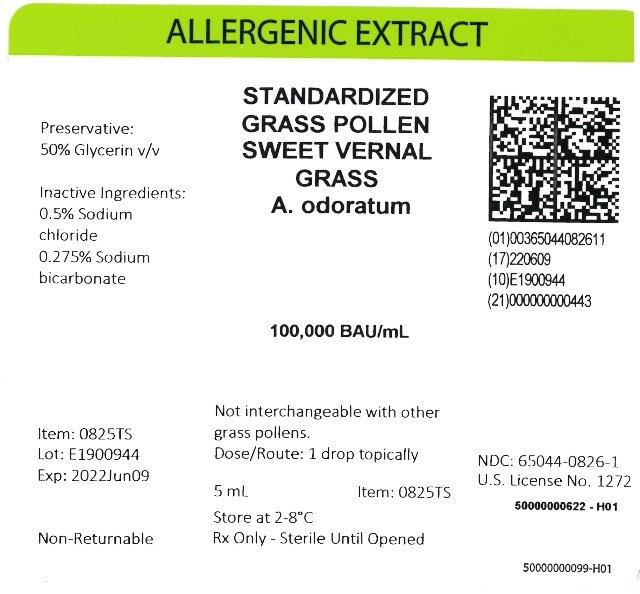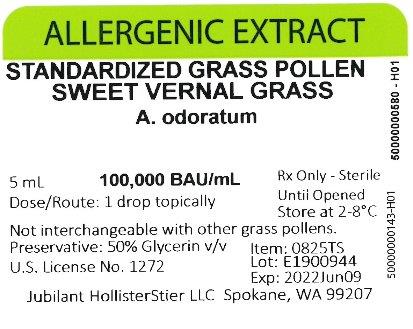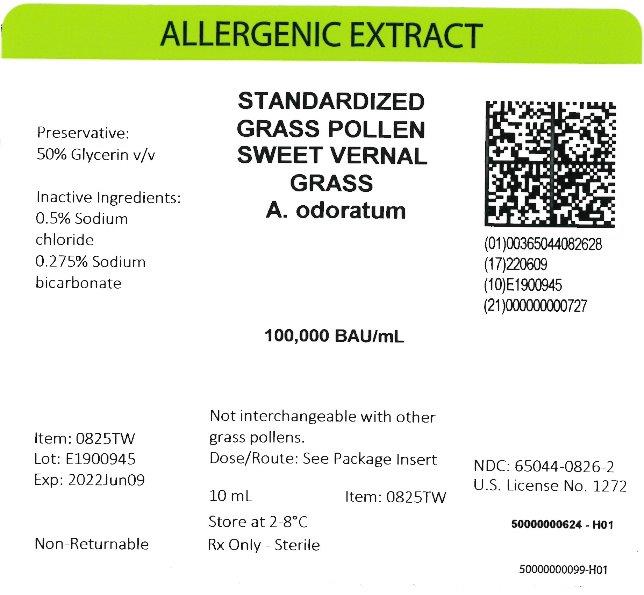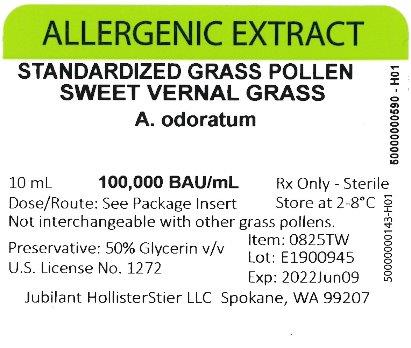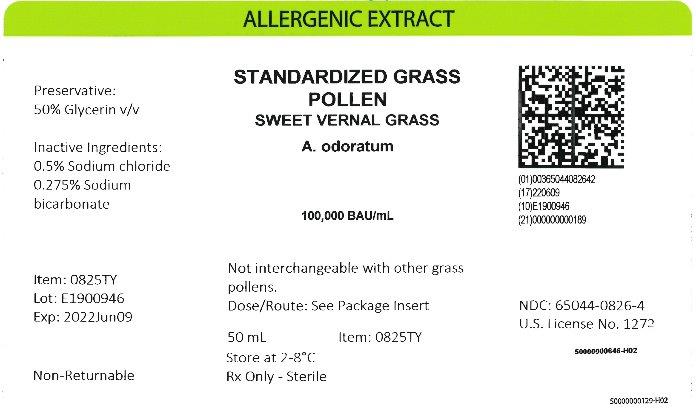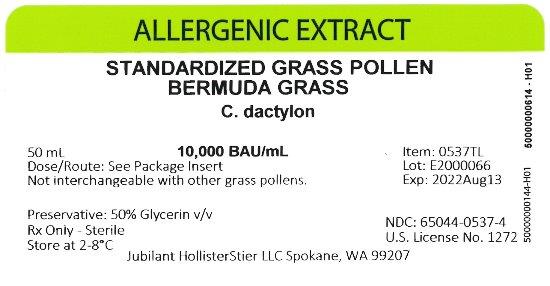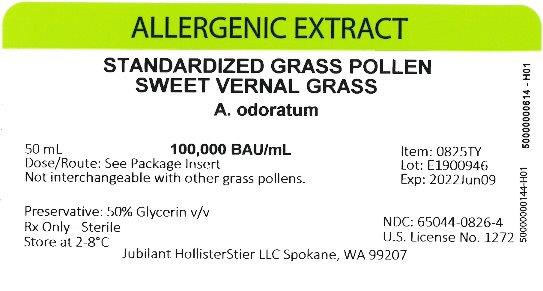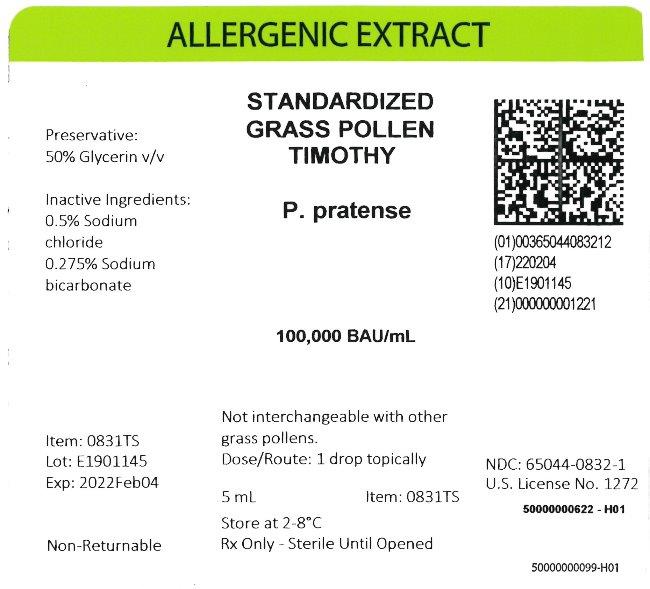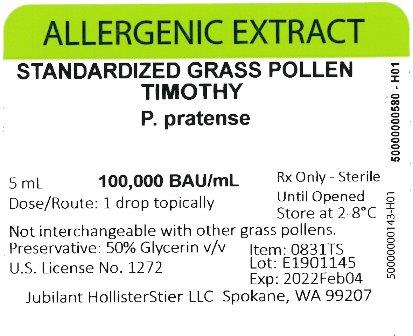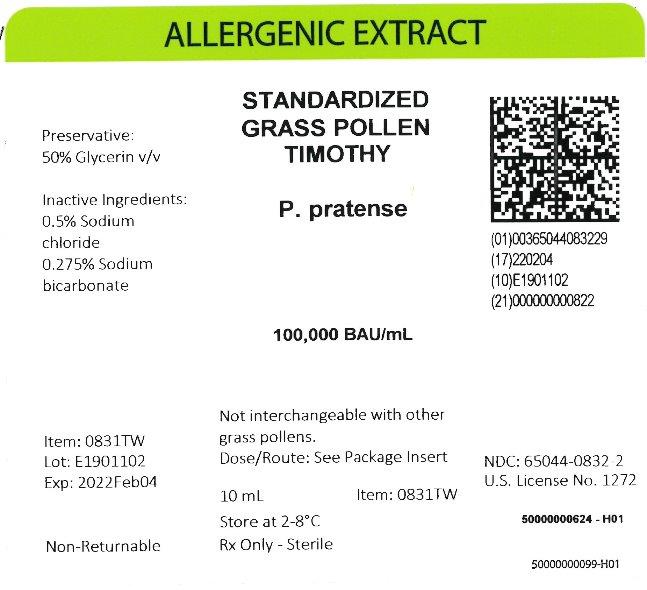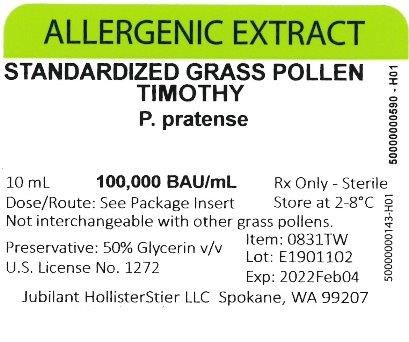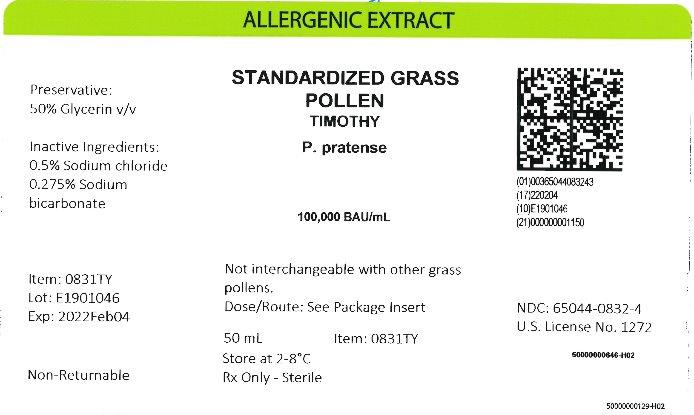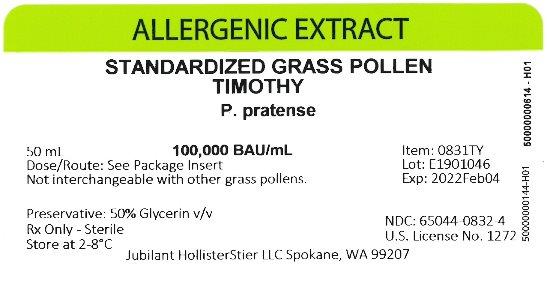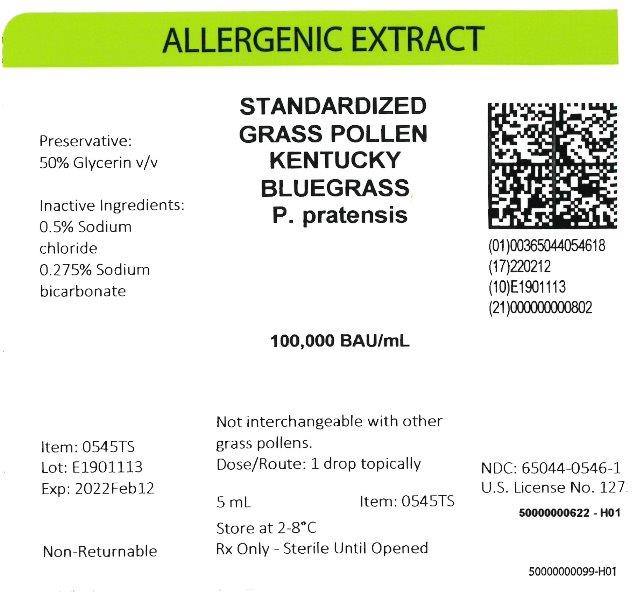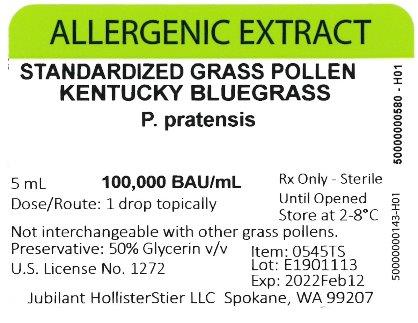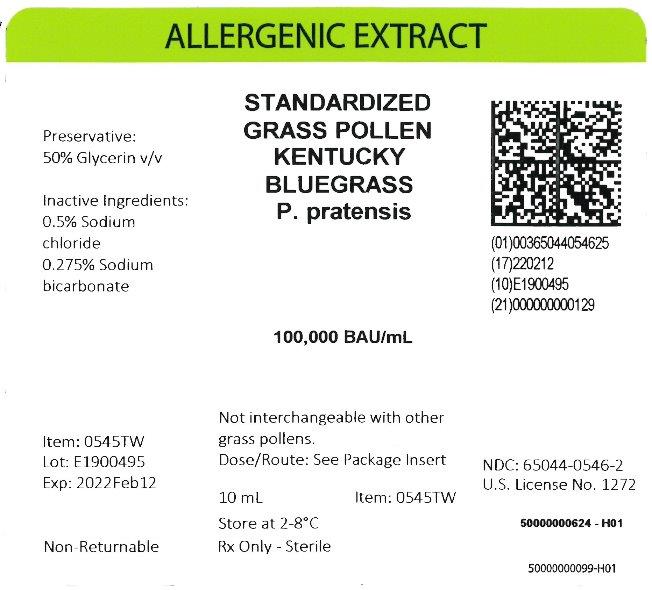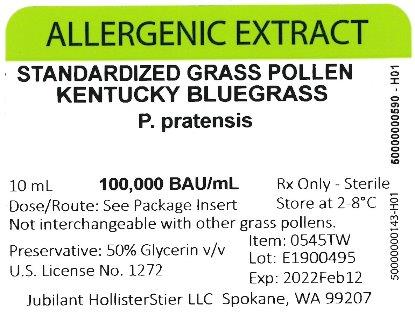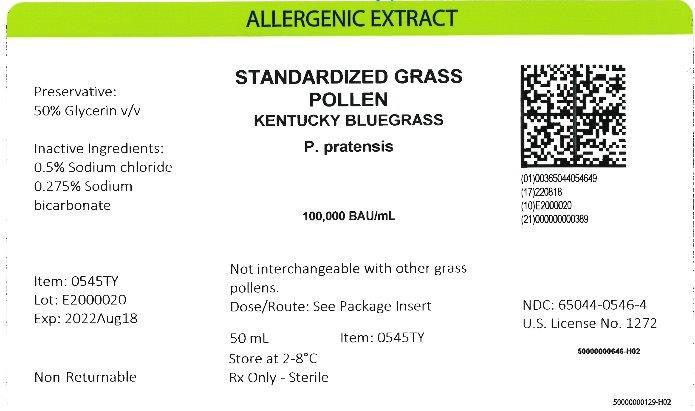 DRUG LABEL: Standardized Grass Pollen, Fescue, Meadow
NDC: 65044-0611 | Form: INJECTION, SOLUTION
Manufacturer: Jubilant HollisterStier LLC
Category: other | Type: STANDARDIZED ALLERGENIC
Date: 20251119

ACTIVE INGREDIENTS: LOLIUM PRATENSE POLLEN 10000 [BAU]/1 mL
INACTIVE INGREDIENTS: GLYCERIN; SODIUM CHLORIDE; SODIUM BICARBONATE

ALLERGENIC EXTRACTS STANDARDIZED GRASS POLLEN (glycerinated)

WARNINGS

This product is intended for use only by licensed medical personnel experienced in administering allergenic extracts and trained to provide immediate emergency treatment in the event of a life-threatening reaction.

Allergenic extracts may potentially elicit a severe life-threatening systemic reaction, rarely resulting in death 1. Therefore, emergency measures and personnel trained in their use must be available immediately in the event of such a reaction. Patients should be instructed to recognize adverse reaction symptoms and cautioned to contact the physician's office if symptoms occur. See ADVERSE REACTION, Section 3, of this insert for information regarding adverse event reporting.
Standardized glycerinated extracts may differ in potency from regular extracts and therefore, are not directly interchangeable with non-standardized extracts, or other manufacturers' products.
Note: BAU/mL Standardized grass pollens are not interchangeable with any other grass pollen products. This product should never be injected intravenously. Patients with cardiovascular diseases or pulmonary diseases such as symptomatic unstable, steroid-dependent asthma, and/or those who are receiving cardiovascular drugs such as beta blockers, may be at higher risk for severe adverse reactions. These patients may also be more refractory to the normal allergy treatment regimen. Patients should be treated only if the benefit of treatment outweighs the risks.1
Refer also to the CONTRAINDICATIONS, WARNINGS, PRECAUTIONS, ADVERSE REACTIONS and OVERDOSE Sections for further discussion.

DESCRIPTION

The grass pollens available in standardized form are: Bermuda Grass (Cynodon dactylon), Orchard Grass (Dactylis glomerata), Perennial Ryegrass (Lolium perenne), Timothy Grass (Phleum pratense), Redtop Grass (Agrostis alba), Kentucky Bluegrass (Poa pratensis), Meadow Fescue (Festuca elatior), and Sweet Vernalgrass (Anthoxanthum odoratum). The pollen extracts are intended for subcutaneous injection for immunotherapy; and intradermal and prick or puncture for diagnosis. Pollen extracts are sterile solutions containing the extractables of pollens, 0.5% Sodium Chloride, 0.275% Sodium Bicarbonate, and 50% Glycerin by volume as a preservative. Sterile, diluted Standardized Grass Pollen Extracts available for intradermal testing contain 0.9% sodium chloride, not more than 0.5% glycerin by volume, 0.03% sodium bicarbonate, and 0.4% phenol as a preservative. Source material for the extracts is collected using techniques such as water set or vacuuming. Source material for allergenic extracts contains no more than a total of 1% of detectable foreign materials (99% pollen purity). Note: BAU/mL Standardized grass pollens are not interchangeable with any other grass pollen products.

Product Concentration:
1. Bioequivalent Allergy Units. These allergenic extracts are labeled in Bioequivalent Allergy Units/mL (BAU/mL) based on their comparison (by ELISA Competition) to Center for Biologics Evaluation and Research (CBER), Food and Drug Administration (FDA) Reference Preparations.2 The FDA reference extracts have been assigned Bioequivalent Allergy Units based on the CBER ID50EAL method.5 Briefly, highly sensitive patients are skin tested to the reference preparation using an intradermal technique employing 3-fold extract dilutions. Depending on the dilution which elicits a summation of erythema diameter of 50mm (D50), Bioequivalent Allergy Units are assigned as follows:

BAU/mL | Intradermal Mean Dilution | D50
1000,000 | 1:5,000,000 | 13-14.9
10,000 | 1:500,000 | 11-12.9
1,000 | 1:50,000 | 9-10.9

The vial potency of Mixtures of Standardized Grasses is calculated by summation of the BAU/mL values of the components of the ingredient list which expresses the potency of each component per mL of the mixture.

2. Concentrate.
a. Concentrate label terminology applies to allergenic extract Custom Mixtures where the individual allergens being combined vary in strength or the designation of strength.

e.g. | Concentrate
50% | Short Ragweed 1:20 w/v
25% | Kentucky Bluegrass 100,000 BAU/mL
25% | Std. Mite D. farinae 10,000 AU/mL

Should the physician choose to calculate the actual strength of each component in the "Concentrate" mixture, the following formulation may be used:

Actual Allergen Strength in Concentrate Mixture | = | Allergen Manufacturing Strength | x | Allergen in Formulation (by volume or parts)

b. In the list of components portion of the product label for Stock Mixtures Containing Standardized Grasses, the potency of each component is calculated to express the potency of each component per 1 mL of the mixture. Vial potency is expressed as concentrate, or as a volume/volume dilution of concentrate.

CLINICAL PHARMACOLOGY

20

The mechanisms by which hyposensitization is achieved are not completely understood. It has been shown that repeated injections of appropriate allergenic extracts will ameliorate the intensity of allergic symptoms upon contact with the allergen.6, 7, 8, 9 Clinical studies which address the efficacy of immunotherapy are available. The allergens which have been studied are cat, mite, and some pollen extracts.10, 11, 12, 13, 14, 15
IgE antibodies bound to receptors on mast cell membranes are required for the allergic reaction, and their level is probably related to serum IgE concentrations. Immunotherapy has been associated with decreased levels of IgE, and also with increases in allergen specific IgG "blocking" antibody.
The histamine release response of circulating basophils to a specific allergen is reduced in some patients by immunotherapy, but the mechanism of this change is not yet clear.
The relationships among changes in blocking antibody, reaginic antibody, and mediator-releasing cells, and successful immunotherapy need study and clarification.
The CBER has evaluated the potency of eight grass pollen extract reference preparations and assigned potency units (BAU/mL) to each.5 The CBER clinical results follow in Table 1. Puncture data were obtained using a bifurcated needle.
Table 1
PUNCTURE AND INTRADERMAL DATA WITH CBER GRASS REFERENCES 3
A. Puncture Data with 10,000 BAU/mL Grass Extracts

 | Sum of Erythema (mm) | Sum of Wheal (mm)
Reference Pollen | N | Mean | Range | Mean | Range
Bermuda Grass - Cynodon dactylon | 15 | 90.3 | 43-123 | 15.7 | 7-31
Kentucky Bluegrass (June) - Poa pratensis | 15 | 77.3 | 47-107 | 15.9 | 6-28
Meadow Fescue - Festuca elatior | 15 | 81.1 | 57-115 | 11.9 | 7-22
Orchard Grass - Dactylis glomerata | 15 | 84.3 | 57-111 | 14.1 | 9-19
Perennial Ryegrass - Lolium perenne | 15 | 92.3 | 73-135 | 17.5 | 6-36
Redtop - Agrostis gigantea (alba) | 15 | 77.1 | 42-98 | 14.1 | 8-19
Sweet Vernalgrass - Anthoxanthum odoratum | 15 | 81.2 | 28-123 | 15.7 | 8-30
Timothy - Phleum pratense | 15 | 88.3 | 51-109 | 16.9 | 8-40

B. Intradermal Dose of CBER Grass References for 50mm Sum of Erythema (BAU50)

Reference Pollen | Mean | BAU50/mL Range
Bermuda Grass - Cynodon dactylon | 0.02 | 0.4-0.0003
Kentucky Bluegrass (June) - Poa pratensis | 0.02 | 0.1-0.004
Meadow Fescue - Festuca elatior | 0.02 | 0.9-0.002
Orchard Grass - Dactylis glomerata | 0.02 | 1.9-0.002
Perennial Ryegrass - Lolium Perenne | 0.02 | 0.7-0.002
Redtop - Agrostis gigantea (alba) | 0.02 | 0.8-0.004
Sweet Vernalgrass - Anthoxanthum odoratum | 0.02 | 1.0-0.002
Timothy - Phleum pratense | 0.02 | 0.6-0.002

TABLE 2

RELATIVE POTENCY OF PREVIOUSLY MANUFACTURED AND DISTRIBUTED NON-STANDARDIZED GRASSES TO CBER REFERENCE STANDARDS
Glycerinated (1:20 w/v) and Non-Glycerinated Pollen Extracts (1:10 w/v)

# of Jubilant HollisterStier LLC Lots Relative to the CBER Reference*
Pollen | # of Lots Tested | Less than | Equal to | Greater Than | Calculated BAU/mL Range** (Rounded to the nearest 000)
Orchard Grass | 20 | 2 | 13 | 5 | 66,000 - 242,000
Perennial Ryegrass | 17 | 5 | 12 | 0 | 25,000 - 127,000
Sweet Vernalgrass | 13 | 1 | 12 | 0 | 73,000 - 110,000
Kentucky Bluegrass | 21 | 8 | 12 | 1 | 32,000 - 145,000
Redtop | 20 | 5 | 6 | 9 | 13,000 - 402,000
Meadow Fescue | 21 | 0 | 1 | 20 | 128,000 - 948,000
Bermuda Grass | 22 | 3 | 13 | 6 | 6,000 - 28,000
Timothy | 19 | 11 | 6 | 2 | 43,000 - 176,000

*All CBER reference extracts contain 100,000 BAU/mL except Bermuda Grass which contains 10,000 BAU/mL.

**BAU/mL ranges between 69,990 and 143,100 are considered equivalent to the CBER 100,000 BAU/mL Standard, and between 6,990 and 14,310 for the CBER 10,000 BAU/mL Standard when assays are done in triplicate.

INDICATIONS AND USAGE

16, 17, 18, 20

Standardized glycerinated allergenic extracts in potencies of 10,000 BAU/mL and 100,000 BAU/mL are indicated for use in diagnosis and immunotherapy of patients presenting symptoms of allergy (hay fever, rhinitis, etc.) to specific grass pollens. Concentrated extracts must be diluted prior to use in intradermal testing and immunotherapy. The selection of allergenic extracts to be used should be based on a thorough and carefully taken history of hypersensitivity, and confirmed by skin testing. 27, 28 10,000 BAU/mL dose form should be used initially for percutaneous testing. If negative, the 100,000 BAU/mL dose can be used.
The use of mixed or unrelated antigens for skin testing is not recommended since, in the case of a positive reaction, it does not indicate which component of the mix is responsible for the reaction, while, in the case of a negative reaction, it fails to indicate whether the individual antigens at full concentration would give a positive reaction. Utilization of such mixes for compounding a treatment may result, in the former case, in administering unnecessary antigens and, in the latter case, in the omission of a needed allergen.
Allergens to which a patient is extremely sensitive should not be included in treatment mixes with allergens to which there is much less sensitivity, but should be administered separately. This allows individualized and better control of dosage increases, including adjustments in dosage becoming necessary after severe reactions which may occur to the highly reactive allergen. Note: BAU/mL Standardized grass pollens are not interchangeable with any other grass pollen products.

CONTRAINDICATIONS

There are no known absolute contraindications to immunotherapy. See PRECAUTIONS for pregnancy risks.
Patients with cardiovascular diseases or pulmonary diseases such as symptomatic unstable, steroid-dependent asthma, and/or those who are receiving cardiovascular drugs such as beta blockers, may be at higher risk for severe adverse reactions. These patients may also be more refractory to the normal allergy treatment regimen. Patients should be treated only if the benefit of treatment outweighs the risks.1
Any injections, including immunotherapy, should be avoided in patients with a bleeding tendency.
Since there are differences of opinion concerning the possibility of routine immunizations exacerbating autoimmune diseases, immunotherapy should be given cautiously to patients with autoimmune diseases, and only if the risk from exposure to the allergen is greater than the risk of exacerbating the autoimmune process.

WARNINGS

See WARNINGS at the beginning of this instruction sheet.

Allergenic extract should be temporarily withheld from patients or the dose adjusted downward if any of the following conditions exist: (1) severe symptoms of rhinitis and/or asthma; (2) infection or flu accompanied by fever; or (3) exposure to excessive amounts of clinically relevant allergen prior to a scheduled injection. Do not start immunotherapy during a period of symptoms due to exposure. Since the individual components of the extract are those to which the patient is allergic, and to which he or she will be exposed, typical allergic symptoms may follow shortly after the injection, particularly when the antigen load from exposure plus the injected antigen exceeds the patient's antigen tolerance. (4) Any evidence of a local or generalized reaction requires a reduction in dosage during the initial stages of immunotherapy, as well as during maintenance therapy.
THE CONCENTRATE SHOULD NOT BE INJECTED AT ANY TIME UNLESS TOLERANCE HAS BEEN ESTABLISHED. DILUTE CONCENTRATED EXTRACTS WITH STERILE ALBUMIN SALINE WITH PHENOL (0.4%) FOR INTRADERMAL TESTING.
INJECTIONS SHOULD NEVER BE GIVEN INTRAVENOUSLY. Subcutaneous injection is recommended. Intracutaneous or intramuscular injections may produce large local reactions or be excessively painful.
AFTER INSERTING NEEDLE SUBCUTANEOUSLY, BUT BEFORE INJECTING, ALWAYS WITHDRAW THE PLUNGER SLIGHTLY. IF BLOOD APPEARS IN THE SYRINGE, CHANGE NEEDLE AND GIVE THE INJECTION IN ANOTHER SITE.

BOXED WARNING

IF CHANGING TO A DIFFERENT LOT OF STANDARDIZED EXTRACT: Even though it is the same formula and concentration, the first dose of the new extract should not exceed 25% to 50% of the last administered dose from the previous extract.

IF THE STANDARDIZED EXTRACT PREVIOUSLY USED WAS FROM ANOTHER MANUFACTURER: Since manufacturing processes and sources of raw materials differ among manufacturers, the interchangeability of extracts from different manufacturers cannot be insured. The starting dose of the standardized glycerinated extract therefore should be greatly decreased even though the extract is the same formula and dilution. Initiate therapy as though patient had not been receiving immunotherapy, or determine initial dose by skin test using serial dilutions of the extract. In highly sensitive individuals, the skin test method may be preferable. See DOSAGE AND ADMINISTRATION and ADVERSE REACTIONS Sections.
IF A PROLONGED PERIOD OF TIME HAS ELAPSED SINCE THE LAST INJECTION: Patients may lose tolerance for allergen injections during prolonged periods between doses. The duration of tolerance is an individual characteristic and varies from patient to patient. In general, the longer the lapse in the injection schedule, the greater dose reduction required. If the interval since last dose is over four weeks, perform skin tests to determine starting dose.
IF THE PREVIOUS EXTRACT WAS OUTDATED: The dating period for allergenic extracts indicates the time that they can be expected to remain potent under refrigerated storage conditions (2°- 8°C). During the storage of extracts, even under ideal conditions, some loss of potency occurs. For this reason, extracts should not be used beyond their expiration date. If a patient has been receiving injections of an outdated extract, he may experience excessive local or systemic reactions when changed to a new, and possibly more potent extract. In general, the longer the material has been outdated, the greater the dose reduction necessary for the fresh extract.
IF THE PREVIOUS EXTRACT WAS NON-STANDARDIZED: Standardized extracts differ in potency from non-standardized extracts. Use Table 2 for guidance in selecting dose for switching. To confirm dose selected, side-by-side skin testing of new and old extracts can be carried out. (See CLINICAL PHARMACOLOGY, Table 2.) Initiate therapy as though the patient had not been receiving immunotherapy, or determine initial dose by skin test using serial dilutions of the extract. See PRECAUTIONS and DOSAGE AND ADMINISTRATION Sections below.
IF ANY OTHER CHANGES HAVE BEEN MADE IN THE EXTRACT CONCENTRATE FORMULA: Changes other than those listed above may include situations such as a redistribution of component parts or percentages, a difference in extracting fluid (i.e., change from non-glycerin extracts to 50% glycerin extracts), combining two or more stock concentrates, or any other change.
It should be recognized that any change in formula can affect a patient's tolerance of the treatment. The usual 1/2 of the previous dose for a new extract may produce an adverse reaction; extra dilutions are recommended whenever starting a revised formula. The greater the change, the greater the number of dilutions required.

WARNINGS

Proper selection of the dose and careful injection should prevent most systemic reactions. It must be remembered, however, that allergenic extracts are highly potent in sensitive individuals, and that systemic reactions of varying degrees of severity may occur, including urticaria, rhinitis, conjunctivitis, wheezing, coughing, angioedema, hypotension, bradycardia, pallor, laryngeal edema, fainting, or even anaphylactic shock and death. Patients should be informed of this, and the precautions should be discussed prior to immunotherapy. (See PRECAUTIONS below.) Severe systemic reactions should be treated as indicated in the ADVERSE REACTIONS Section below.

PRECAUTIONS

1. GENERAL

The presence of asthmatic signs and symptoms appear to be an indicator for severe reactions following allergy injections. An assessment of airway obstruction either by measurement of peak flow or an alternate procedure may provide a useful indicator as to the advisability of administering an allergy injection.1, 30, 31, 32, 33
Concentrated extracts must be diluted prior to use: See DOSAGE AND ADMINISTRATION Section for detailed instructions on the dilution of standardized glycerinated allergenic extracts.
Allergenic extracts diluted with Albumin Saline with Phenol (0.4%) may be more potent than extracts diluted with diluents which do not contain stabilizers. When switching from non-stabilized to stabilized diluent, consider weaker initial dilutions for both intradermal testing and immunotherapy.
Sterile solutions, vials, syringes, etc. should be used and aseptic precautions observed in making dilutions.
To avoid cross-contamination, do not use the same needle to withdraw materials from vials of more than one extract, or extract followed by diluent.
A sterile tuberculin syringe graduated in 0.01 mL units should be used to measure each dose from the appropriate dilution. Aseptic techniques should always be employed when injections of allergenic extracts are being administered.
A separate sterile syringe should be used for each patient to prevent transmission of hepatitis and other infectious agents from one person to another.
Patient reactions to previous injections should be reviewed before each new injection. A conservative dosage schedule should be followed by the physician until a pattern of local responses is established which can be used to monitor increases in dosage.
Rarely, a patient is encountered who develops systemic reactions to minute doses of allergen and does not demonstrate increasing tolerance to injections after several months of treatment. If systemic reactions or excessive local responses occur persistently at very small doses, efforts at immunotherapy should be stopped.
PATIENTS SHOULD BE OBSERVED IN THE OFFICE FOR AT LEAST 30 MINUTES AFTER EACH TREATMENT INJECTION. Most severe reactions will occur within this time period, and rapid treatment measures should be instituted. See ADVERSE REACTIONS Section for such treatment measures.

2. INFORMATION FOR PATIENTS

Patients should be instructed in the recognition of adverse reactions to immunotherapy, and in particular, to the symptoms of shock. Patients should be made to understand the importance of a 30 minute observation period, and be warned to return to the office promptly if symptoms occur after leaving.

3. CARCINOGENESIS, MUTAGENESIS, IMPAIRMENT OF FERTILITY

Long-term studies in animals have not been conducted with allergenic extracts to determine their potential for carcinogenicity, mutagenicity or impairment of fertility.

4. PREGNANCY

29

Allergenic Extracts. Animal reproduction studies have not been conducted with allergenic extracts. It is also not known whether allergenic extracts can cause fetal harm when administered to a pregnant woman or can affect reproduction capacity. Allergenic extracts should be given to a pregnant woman only if clearly needed. For women who have been getting maintenance doses of allergen without side effect, the occurrence of pregnancy is not an indication to stop immunotherapy.

5. NURSING MOTHERS

There are no current studies on secretion of the allergenic extract components in human milk, or of their effect on the nursing infant. Because many drugs are excreted in human milk, caution should be exercised when allergenic extracts are administered to a nursing woman.

6. PEDIATRIC USE

Since dosage for the pediatric population is the same as for adults,21 the larger volumes of solution may produce excessive discomfort. Therefore, in order to achieve the total dose required, the volume of the dose may need to be divided into more than one injection per visit.

7. GERIATRIC USE

The reactions from immunotherapy can be expected to be the same in elderly patients as in younger ones. Elderly patients may be more likely to be on medication that could block the effect of epinephrine which could be used to treat serious reactions, or they could be more sensitive to the cardiovascular side effect of epinephrine because of pre-existing cardiovascular disease.4

8. DRUG INTERACTIONS

Patients on non-selective beta blockers may be more reactive to allergens given for diagnosis or treatment, and may be unresponsive to the usual doses of epinephrine used to treat allergic reactions.19
Certain medications may lessen the skin test wheal and erythema responses elicited by allergens and histamine for varying time periods. Conventional antihistamines should be discontinued at least 5 days before skin testing. Long acting antihistamines should be discontinued for at least 3 weeks prior to skin testing.23 Topical steroids should be discontinued at the skin test site for at least 2-3 weeks before skin testing.23, 24 Tricyclic antidepressants such as Doxepin should be withheld for at least 7 days before skin testing.25 Topical local anesthetics may suppress the flare responses and should be avoided in skin test sites.26

ADVERSE REACTIONS

1. Local Reactions
Some erythema, swelling or pruritus at the site of injection are common, the extent varying with the patient. Such reactions should not be considered significant unless they persist for at least 24 hours. Local reactions (erythema or swelling) which exceed 4-5 cm in diameter are not only uncomfortable, but also indicate the possibility of a systemic reaction if dosage is increased. In such cases the dosage should be reduced to the last level not causing the reaction and maintained at this level for two or three treatments before cautiously increasing again.
Large persistent local reactions may be treated by local cold, wet dressings and/or the use of oral antihistamines. They should be considered a warning of possible severe systemic reactions and an indication of the need for temporarily reduced dosages.
A mild burning immediately after the injection is to be expected. This usually leaves in 10 to 20 seconds.

2. Systemic Reactions
With careful attention to dosage and administration, systemic reactions occur infrequently, but it cannot be overemphasized that in sensitive individuals, any injection could result in anaphylactic shock. Therefore, it is imperative that physicians administering allergenic extracts understand and be prepared for the treatment of severe reactions.
Other possible systemic reactions which may occur in varying degrees of severity are laryngeal edema, fainting, pallor, bradycardia, hypotension, angioedema, cough, wheezing, conjunctivitis, rhinitis, and urticaria. Adverse reaction frequency data for allergenic extract administration for testing and treatment show that risk is low.1, 22
If a systemic or anaphylactic reaction does occur, apply a tourniquet above the site of injection and inject 1:1,000 epinephrine-hydrochloride intramuscularly or subcutaneously into the opposite arm. Loosen the tourniquet at least every 10 minutes. Do not obstruct arterial blood flow with the tourniquet.
EPINEPHRINE DOSAGE
ADULT DOSAGE: 0.3 to 0.5 mL should be injected. Repeat in 5 to 10 minutes if necessary.
PEDIATRIC DOSAGE: The usual initial dose is 0.01 mg (mL) per kg body weight or 0.3 mg (mL) per square meter of body surface area. Suggested dosage for infants to 2 years of age is 0.05 to 0.1 mL; for children 2 to 6 years, 0.15 mL; and children 6 to 12 years, 0.2 mL. Single pediatric doses should not exceed 0.3 mg (mL). Doses may be repeated as frequently as every 20 minutes, depending on the severity of the condition and the response of the patient.
After administration of epinephrine, profound shock or vasomotor collapse should be treated with intravenous fluids, and possibly vasoactive drugs. Airway patency should be insured. Oxygen should be given by mask. Intravenous antihistamines, inhaled bronchodilators, theophylline and/or corticosteroids may be used if necessary after adequate epinephrine and circulatory support have been given. Emergency resuscitation measures and personnel trained in their use must be available immediately in the event of a serious systemic or anaphylactic reaction not responsive to the above measures
[Ref. J.Allergy and Clinical Immunology, 77(2): p. 271-273, 1986].
Rarely are all of the above measures necessary; the tourniquet and epinephrine usually produce prompt responses. However, the physician should be prepared in advance for all contingencies. Promptness in beginning emergency treatment measures is of utmost importance.
Severe systemic reactions mandate a decrease of at least 50% in the next dose, followed by cautious increases. Repeated systemic reactions, even of a mild nature, are sufficient reason for the cessation of further attempts to increase the reaction-causing dose.

3. Adverse Event Reporting
Report all adverse events to Jubilant HollisterStier LLC Customer Technical Services Department at 1 (800) 992-1120. A voluntary adverse event reporting system for health professionals is available through the FDA MEDWATCH program. Preprinted forms (FDA Form 3500) are available from the FDA by calling 1 (800) FDA-1088. Completed forms should be mailed to MEDWATCH, 5600 Fisher Lane, Rockville, MD 20852-9787 or Fax to: 1 (800) FDA-0178.

OVERDOSAGE

See ADVERSE REACTIONS Section.

DOSAGE AND ADMINISTRATION

1. General
Sterile aqueous diluent containing albumin (human) [Albumin Saline with Phenol (0.4%)] or diluent of 50% glycerin may be used when preparing dilutions of the concentrate for immunotherapy. For intradermal testing dilutions, Albumin Saline with Phenol (0.4%) is recommended.
Dilutions should be made accurately and aseptically, using sterile diluent, vials, syringes, etc. Mix thoroughly and gently by rocking or swirling.
Parenteral drug products should be inspected visually for particulate matter and discoloration prior to administration whenever solution and container permit.

2. Diagnosis
Prick or Puncture Test: To identify highly sensitive individuals and as a safety precaution, it is recommended that a prick or puncture test using a drop of 10,000 BAU/mL extract be performed prior to initiating intradermal testing. If this test is negative, a second prick/puncture test may be performed using a 100,000 BAU/mL extract. Prick tests are performed by placing a drop of extract on the skin and piercing through the drop into the skin with a slight lifting motion. Puncture tests are performed by placing a drop of extract concentrate on the skin and piercing the skin through the drop with a small needle such as a Prick Lancetter. Fifteen minutes after puncture is made the diameter of wheal and erythema reactions are measured, and the sensitivity class of the patient determined by Table 3. Less sensitive individuals (Class 0 to 1+) can be tested intradermally with the recommended dilutions of the extract concentrate (See intradermal testing instructions).
Intradermal Test: Patients with a negative prick or puncture test should be tested intradermally with 100 BAU/mL. If this test is negative, a second intradermal test may be performed using a 1,000 BAU/mL extract. The negative control should have glycerin concentration equivalent to the glycerin concentration of the intradermal test solution, not to exceed 5% glycerin.
It is recommended that patients be tested using the intradermal technique only after screening by prick or puncture test.
Extract for intradermal testing should be prepared by diluting the stock concentrate, provided in multiple-dose vials, with Sterile Albumin Saline with Phenol (0.4%) (refer to Table 4 in the Immunotherapy section below).
To administer the intradermal strength dilutions, a 1 mL tuberculin syringe with a short 27-gauge needle should be used. The needle is inserted intradermally at a 30° angle, bevel down, and 0.02 to 0.05 mL of the extract is injected. Fifteen minutes following injection, the diameter of wheal and erythema reactions are measured, and the patient's sensitivity class is determined by the table below. Skin tests are graded in terms of the wheal and erythema response noted at 10 to 20 minutes. Wheal and erythema size may be recorded by actual measurement of the extent of both responses. Refer to Table 3 to determine the skin test sensitivity class. The corresponding ∑E (sum of the longest diameter and the mid-point orthogonal diameters of erythema) is also presented.

TABLE 3 Classification of Skin Test Sensitivity for Intradermal and Pick or Puncture

Class | Wheal Diameter | Erythema Diameter | Corresponding ∑E
0 | < 5 mm | <5 mm | <10 mm
± | 5-10 mm | 5-10 mm | 10-20 mm
1+ | 5-10 mm | 11-20 mm | 20-40 mm
2+ | 5-10 mm | 21-30 mm | 40-60 mm
3+ | 10-15 mm a | 31-40 mm | 60-80 mm
4+ | >15 mm b | >40 mm | >80 mm

a. or with pseudopods

b. or with many pseudopods

3. Immunotherapy
Allergenic extracts should be administered using a sterile syringe with 0.01 mL gradations and a 25-27 gauge X 1/2" to 5/8" needle. The injections are given subcutaneously. The most common sites of injection are the lateral aspect of the upper arm or thigh. Intracutaneous or intramuscular injections may produce large local reactions which may be very painful.
Dosage of allergenic extracts is a highly individualized matter and varies according to the degree of sensitivity of the patient, his clinical response, and tolerance to the extract administered during the early phases of an injection regimen. The starting dose should be based on skin tests of the extract to be used for immunotherapy. To prepare dilutions for intradermal and therapeutic use, make a 1:10 dilution by adding 1.0 mL of the concentrate to 9.0 mL of Sterile Albumin Saline with Phenol (0.4%). Subsequent serial dilutions are made in a similar manner. (See Table 4.) To determine the starting dose, begin intradermal testing with the most dilute extract preparation. Inject 0.02 mL and read the reaction after 15 minutes. Intradermal testing is continued with increasing concentrations of the extract until a reaction of 11-20 mm erythema ∑E 20-40 mm) and/or a 5 mm wheal occurs. This concentration at a dose of 0.03 mL then can serve as a starting dose for immunotherapy and be increased by 0.03 mL to as high as 0.12 mL increments each time until 0.3 mL is reached, at which time a dilution 10 times as strong can be used, starting with 0.03 mL. Proceed in this way until a tolerance dose is reached or symptoms are controlled. Suggested maintenance dose is 0.2 mL of the concentrate. Occasionally, higher doses are necessary to relieve symptoms. Special caution is required in administering doses greater than 0.2 mL. The interval between doses normally is 3 to 7 days.
Potencies of 10,000 BAU/mL and 100,000 BAU/mL are available for treatment. The two selections are available to facilitate safe switching by providing flexibility in dosing. For previously untreated patients, initiate treatment using dilutions made from the 10,000 BAU/mL concentrate. If tolerated and symptoms justify a higher dosage, then use of dilutions made from the 100,000 BAU/mL concentrate is warranted. Proceed with caution when using 100,000 BAU/mL in higher doses.
When converting a patient who is currently receiving non-standardized grass pollen extracts, it is recommended that skin testing be performed to compare the potency of the new and old extracts. If you choose not to skin test as recommended, but to continue therapy, the maximum first dose of the new allergenic product should not exceed 10% (1/10) of the previous dose.
This is offered as a suggested schedule for average patients and will be satisfactory in most cases. However, the degree of sensitivity varies in many patients. The size of the dose should be adjusted and should be regulated by the patient's tolerance and reaction. The size of the dose should be decreased if the previous injection resulted in marked local or the slightest general reaction. Another dose should never be given until all local reactions resulting from the previous dose have disappeared.
In some patients, the dosage may be increased more rapidly than called for in the schedule. In seasonal allergies, treatment should be started and the interval between doses regulated so that at least the first twenty doses will have been administered by the time symptoms are expected. Thus, the shorter the interval between the start of immunotherapy and the expected onset of symptoms, the shorter the interval between each dose. Some patients may even tolerate daily doses. A maintenance dose, the largest dose tolerated by the patient that relieves symptoms without producing undesirable local or general reactions, is recommended for most patients. The upper limits of dosage have not been established; however, doses larger than 0.2 mL of the glycerin concentrate may be painful due to the glycerin content. The dosage of allergenic extract does not vary significantly with the respiratory allergic disease under treatment. The size of this dose and the interval between doses will vary and can be adjusted as necessary. Should symptoms develop before the next injection is scheduled, the interval between doses should be decreased. Should allergic symptoms or local reactions develop shortly after the dose is administered, the size of the dose should be decreased. In seasonal allergies, it is often advisable to decrease the dose to one-half or one-quarter of the maximum dose previously attained if the patient has any seasonal symptoms.
The interval between maintenance doses can be increased gradually from one week to 10 days, to two weeks, to three weeks, or even to four weeks if tolerated. Repeat the doses at a given interval three or four times to check for untoward reactions before further increasing the interval. Protection is lost rapidly if the interval between doses is more than four weeks. (See WARNINGS Section.)
The usual duration of treatment has not been established. A period of two or three years of injection therapy constitutes an average minimum course of treatment.

TABLE 4
TEN-FOLD DILUTION SERIES
Standardized Extracts Labeled 100,000 BAU/mL
Dilution | Extract | + Diluent | = | BAU/mL Concentration
0 | Concentrate | +0 mL | = | 100,000
1 | 1 mL Concentrate | +9 mL | = | 10,000
2 | 1 mL dilution #1 | +9 mL | = | 1,000
3 | 1 mL dilution #2 | +9 mL | = | 100
4 | 1 mL dilution #3 | +9 mL | = | 10
5 | 1 mL dilution #4 | +9 mL | = | 1.0
6 | 1 mL dilution #5 | +9 mL | = | 0.10
7 | 1 mL dilution #6 | +9 mL | = | 0.010

(4) PEDIATRIC USE

The dose for the pediatric population is the same as for adults. (See PRECAUTIONS.)

(5) GERIATRIC USE

The dose for elderly patients is the same as for adult patients under 65.4

HOW SUPPLIED

Standardized allergenic extracts of grass pollens are supplied for diagnostic and therapeutic use:

Diagnostics:
Extracts: Pollens*
Prick/puncture tests, 10,000 BAU/mL and 100,000 BAU/mL [50% glycerin (v/v)] in 5 mL dropper vial.
Intradermal Tests [Aqueous] of 100 BAU/mL in 5 mL vial, and 1,000 BAU/mL in 5 mL vial.
(Intradermal test solutions may contain up to 5% glycerin.)
*Bermuda grass, 10,000 BAU/mL is highest concentration.
Bulk Therapeutics [50% glycerin (v/v)] in multiple dose vials:
Extracts: Pollens*
10 mL vial, in strengths of 100,000 BAU/mL and 10,000 BAU/mL
30 mL vial, in strengths of 100,000 BAU/mL and 10,000 BAU/mL
50 mL vial, in strengths of 100,000 BAU/mL and 10,000 BAU/mL
*Bermuda grass, 10,000 BAU/mL only.

STORAGE

The expiration date of pollen extract in 50% glycerin is listed on the container label. The extract should be stored at 2°- 8°C. Dilutions containing less than 50% glycerin are less stable and, if loss of potency is suspected, should be checked by skin testing with equal units of a freshly prepared dilution on known pollen allergic individuals. The expiration date of the intradermal tests is listed on container labels. Store at 2°- 8°C.

LIMITED WARRANTY

A number of factors beyond our control could reduce the efficacy of this product or even result in an ill effect following its use. These include storage and handling of the product after it leaves our hands, diagnosis, dosage, method of administration and biological differences in individual patients. Because of these factors, it is important that this product be stored properly and that the directions be followed carefully during use. No warranty, express or implied, including any warranty of merchantability or fitness, is made. Representatives of the Company are not authorized to vary the terms or the contents of any printed labeling, including the package insert, for this product except by printed notice from the Company's headquarters. The prescriber and user of this product must accept the terms hereof.

REFERENCES

1. Lockey, Richard F., Linda M. Benedict, Paul C. Turkeltaub, Samuel C. Bukantz. Fatalities from immunotherapy (IT) and skin testing (ST). J. Allergy Clin. Immunol., 79 (4): 660-677, 1987.
2. U.S. Food and Drug Administration (FDA), Center for Biologics Evaluation and Research (CBER). ELISA competition assay (Enzyme-linked Immunosorbent Assay). Methods of Allergenic Products Testing Laboratory. October 1993. CBER Docket No. 94N.0012.
3. U.S. Food and Drug Administration, Center for Biologics Evaluation and Research, Data on file.
4. Peebles, Ray Stokes, Jr., B. Bochner, Howard J. Zeitz, ed. Anaphylaxis in the elderly. Immunology and Allergy Clinics of North America. 13 (3): 627-646, August 1993.
5. Turkeltaub, P., S. Rastogi. Quantitative intradermal test procedure for evaluation of subject sensitivity to standardized allergenic extracts and for assignment of bioequivalent allergy units to reference preparations using the ID50EAL method, Allergenic Products Testing Laboratory, Center for Biologics Evaluation and Research (CBER), FDA. Revised November 1994.
6. Lowell, F. C., W. Franklin. A "double-blind" study of treatment with aqueous allergenic extracts in cases of allergic rhinitis. J. Allergy, 34 (2): 165-182, 1983.
7. Lowell, F. C., W. Franklin. A double-blind study of the effectiveness and specificity of injection therapy in ragweed hay fever. N. Eng. J. Med., 273 (13): 675-679, 1965.
8. Zavazal, V., A. Stajner. Immunologic changes during specific treatment of the atopic state. II. Acta. Allergol., 25 (1): 11-17, 1970.
9. Reisman, R.E., J.I. Wypych, E.E. Arbesman. Relationship of immunotherapy, seasonal pollen exposure and clinical response to serum concentrations of total IgE and ragweed-specific IgE. Int. Arch. Allergy Appl. Immunol., 48 (6): 721-730, 1975.
10. Taylor, W.W., J.L. Ohman, F. C. Lowell. Immunotherapy in cat-induced asthma; double-blind trial with evaluation of bronchial responses to cat allergen and histamine. J. Allergy and Clin. Immunol., 61 (5): 283-287, 1978.
11. Smith, A. P. Hyposensitization with Dermatophagoides pteronyssinus antigen: trial in asthma induced by house dust. Br. Med. J., 4: 204-206, 1971.
12. Chapman, M.D., T.A.E. Platts-Mills, M. Gabriel, H.K. Ng, W. G. L. Allen, L. E. Hill, A. J. Nunn. Antibody response following prolonged hyposensitization with Dermatophagoides pteronyssinus extract. Int. Arch. Allergy Appl. Immunol., 61: 431-440, 1980.
13. Norman, P.S. Postgraduate Course Presentation. An overview of immunotherapy, implications for the future. J. Allergy Clin. Immunol., 65 (2): 87-96, 1980.
14. Norman, P.S., W. L. Winkenwerder. Maintenance immunotherapy in ragweed hay fever. J. Allergy, 74: 273-282, 1971.
15. Norman, P.S., W. L. Winkenwerder, L. M. Lichtenstein. Immunotherapy of hay fever with ragweed antigen E; comparisons with whole pollen extract and placebos. J. Allergy, 42: 93-108, 1968.
16. Sheldon, J. M., R. G. Lovell, K. P. Matthews. A Manual of Clinical Allergy. Second Edition. W.B. Saunders, Philadelphia, 1967, pp. 107-112.
17. Sherman, W. B. Hypersensitivity mechanism and management. W. B. Sanders, Philadelphia, 1968, pp. 169-172.
18. Swineford, O. Asthma and Hay Fever. Charles C. Thomas, Springfield, IL, 1971, pp. 148-155.
19. Jacobs, R. L., G. W. Rake, Jr., et al. Potentiated anaphylaxis in patients with drug-induced beta-adrenergic blockade. J. Allergy and Clin. Immunol., 68 (2): 125-127, August 1981.
20. Patterson, Roy, et al. Allergy Principles and Practice, 2nd ed. E. Middleton, Jr., C.E. Reed, E.F. Ellis, Ed., C.V. Mosby Co., 1983, St. Louis, MO, 1983, Chapter 52.
21. Levy, D.A., L.M. Lichtenstein, E.O. Goldstein, and K. Ishizaka. Immunologic and cellular changes accompanying the therapy of pollen allergy. J. Clinical Investigation, 50:360, 1971.
22. Turkeltaub, Paul C., MD, and Peter J. Gergen, MD. The risk of adverse reactions from percutaneous prick-puncture allergen skin testing, venipuncture, and body measurements: data from the Second National Health and Nutrition Examination Survey, 1976-80 (NHANES II). J. Allergy Clin. Immunol. 84(6): 886-890, Dec. 1989.
23. Pipkorn, Ulf. Pharmacological influence of anti-allergic medication on In Vivo allergen testing. Allergy. 43: 81-86, 1988.
24. Andersson, M. and U. Pipkorn. Inhibition of the dermal immediate allergic reaction through prolonged treatment with topical glucocorticosteroids. J. Allergy Clin. Immunol. 79 (2): 345-349, Feb. 1987.
25. Rao, Kamineni S., et al. Duration of suppressive effect of tricyclic anti-depressants on histamine induced wheal and flare reactions on human skin. J. Allergy Clin. Immunol. 82: 752-757, November 1988.
26. Pipkorn, Ulf, and M. Andersson. Topical dermal anesthesia inhibits the flare but not the wheal response to allergen and histamine in the skin prick test. Clinical Allergy. 17: 307-311, 1987.
27. Pauli, G., J.C. Bessot, R. Thierry and A. Lamensons. Correlation between skin, inhalation tests and specific IgE in a study of 120 subjects to house dust and D. pteronyssinus. Clin. Allergy. 7:337, 1977.
28. Murray, A.B., A.C. Ferguson and B.J. Morrison. Diagnosis of house dust mite allergy in asthamatic children. What constitutes positive history? J. Allergy Clin. Immunol. 71: 21, 1983.
29. Metzger, W.J., E. Turner and R. Patterson. The safety of immunotherapy during pregnancy. J. Allergy Clin. Immunol. 61 (4): 268-272, 1978.
30. Reid, M.J., R.F. Lockey, P.C. Turkletaub, T.A.E. Platts-Mills. Survey of fatalities from skin testing and immunotherapy. J. Allergy Clin. Immunol. 92 (1): 6-15, July 1993.
31. Reid, M.J., G. Gurka. Deaths associated with skin testing and immunotherapy. J. Allergy Clin. Immunol. 97(1) Part 3:231, Abstract 195, January 1996.
32. Thompson, R.A. et al, report of a WHO/IUIS working group. The current status of allergen immunotherapy (hyposensitization). Allergy. 44: 369-379, 1989.
33. Malling, H.-J., B. Weeke, et al, The European Academy of Allergology and Clinical Immunology. Position Papers. Allergy. 48 (Supplement 14): 9-82, 1993.